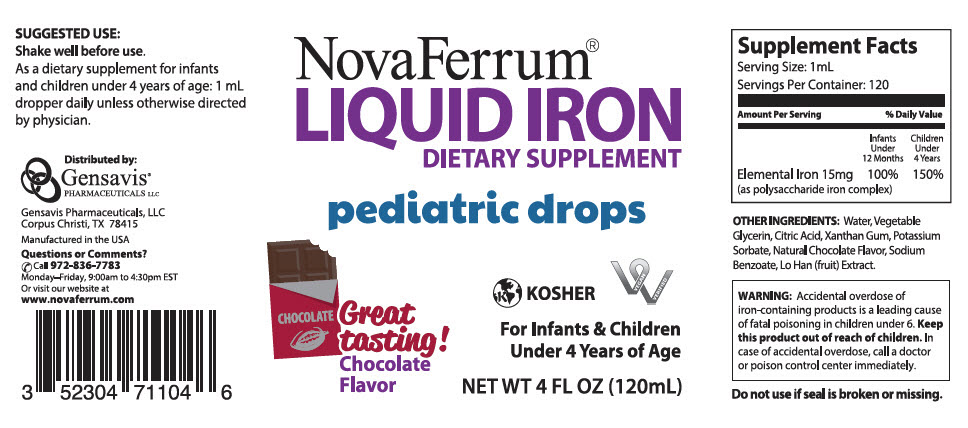 DRUG LABEL: NovaFerrum
NDC: 52304-711 | Form: LIQUID
Manufacturer: Gensavis Pharmaceuticals, LLC
Category: other | Type: DIETARY SUPPLEMENT
Date: 20180801

ACTIVE INGREDIENTS: iron 15 mg/1 mL
INACTIVE INGREDIENTS: water; CITRIC ACID MONOHYDRATE; Xanthan Gum; Potassium Sorbate; Sodium Benzoate; SIRAITIA GROSVENORII FRUIT

NovaFerrum® LIQUID IRON DIETARY SUPPLEMENT

STATEMENT OF IDENTITY

Supplement Facts
Serving Size: 1mL
Servings Per Container: 120
Amount Per Serving | % Daily Value
 | Infants Under 12 Months | Children Under 4 Years
Elemental Iron 15mg (as polysaccharide iron complex) | 100% | 150%

OTHER INGREDIENTS: Water, Vegetable Glycerin, Citric Acid, Xanthan Gum, Potassium Sorbate, Natural Chocolate Flavor, Sodium Benzoate, Lo Han (fruit) Extract.

WARNINGS

WARNING: Accidental overdose of iron-containing products is a leading cause of fatal poisoning in children under 6. Keep this product out of reach of children. In case of accidental overdose, call a doctor or poison control center immediately.

Do not use if seal is broken or missing.

SUGGESTED USE

Shake well before use.

As a dietary supplement for infants and children under 4 years of age: 1 mL dropper daily unless otherwise directed by physician.

HEALTH CLAIM

Distributed by:

Gensavis Pharmaceuticals, LLC
Corpus Christi, TX 78415

Manufactured in the USA

Questions or Comments?
Call 972-836-7783
Monday–Friday, 9:00am to 4:30pm EST
Or visit our website at
www.novaferrum.com

PRINCIPAL DISPLAY PANEL - 120 mL Bottle Label

NovaFerrum®
LIQUID IRON
DIETARY SUPPLEMENT

pediatric drops

Great
tasting!
Chocolate
Flavor

KOSHER

VEGAN
VERIFIED

For Infants & Children
Under 4 Years of Age

NET WT 4 FL OZ (120mL)